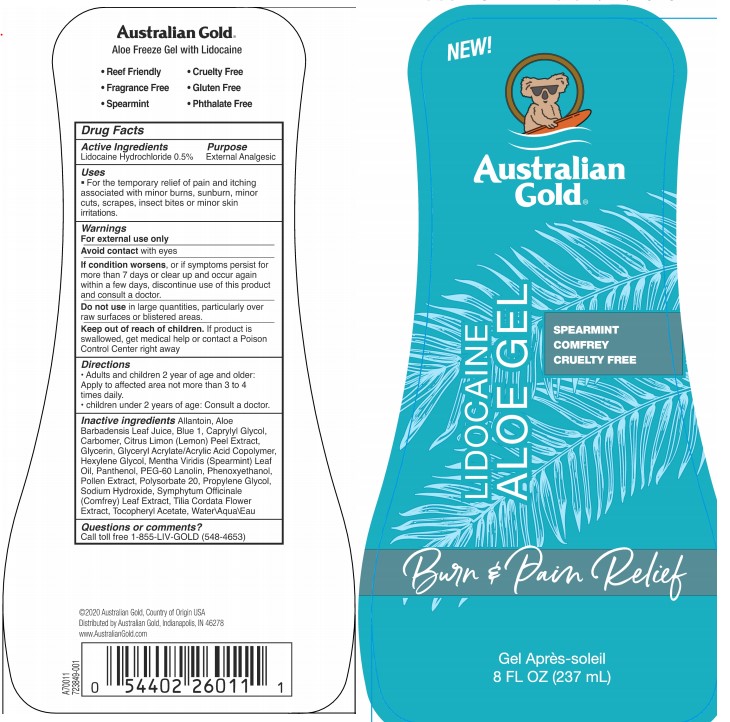 DRUG LABEL: Australian Gold
NDC: 58443-0327 | Form: GEL
Manufacturer: Prime Enterprises, Inc.
Category: otc | Type: HUMAN OTC DRUG LABEL
Date: 20200512

ACTIVE INGREDIENTS: LIDOCAINE 5.05 mg/1 mL
INACTIVE INGREDIENTS: SODIUM HYDROXIDE; HEXYLENE GLYCOL; ALOE VERA LEAF; FD&C BLUE NO. 1; CARBOMER HOMOPOLYMER TYPE C (ALLYL PENTAERYTHRITOL CROSSLINKED); POLYSORBATE 20; PROPYLENE GLYCOL; WATER; CAPRYLYL GLYCOL; PHENOXYETHANOL; PANTHENOL; ALLANTOIN; SCOTCH SPEARMINT OIL; PEG-60 LANOLIN; CITRUS BIOFLAVONOIDS; BEE POLLEN; COMFREY LEAF; TILIA CORDATA FLOWER; ALPHA-TOCOPHERYLQUINONE; GLYCERIN; CARBOMER 1342

Australian Gold Lidocaine ALOE GEL

Active ingredients

Lidocaine Hydrochloride(0.5 %)

Purpose

External Analgesic

Indications

For the temporary relief of pain and itching associated with minor burns, sunburn, minor cuts, scrapes, insect bites or minor skin irritations.

Warnings

For external use only

Avoid contact with eyes

if condition worsens, or if symptoms persist for more than 7 days or clear up and occur again within a few days, discontinue use of this product and consult a doctor

Do not use in large quantities, particularly over raw surfaces or bliseterd areas

Keep out of reach of children. if product is swallowed, get medical help or contact a poison control center right away.

OTHER SAFETY INFORMATION

For external use only.

WHEN USING

Avoid contact with eyes.

STOP USE

If conditions worsens, or is symptoms persist for more than 7 days or clear up and occur again within a few days, discontinue use of this product and consult a doctor.

Do not use in large quantities, particularly over raw surfaces or blistered areas.

Keep out of reach of children. If product is swallowed, get medical help or contact a Poison Control Center right away

Directions

- Adults and children 2 years of age and older:

Apply to afftected area not more than 3 to 4 times daily.

- Children under 2 years of age:

consult a doctor.

Inactive Ingredients

Allantoin, Aloe Barbadensis Leaf Juice, Blue 1, Caprylyl Glycol, Carbomer, Citrus Limon (Lemon) Peel Extract, Glycerin, Glyceryl Acrylate/Acrylic Acid Copolymer, Hexylene Glycol, Mentha Viridis (Spearmint) Leaf Oil, Panthenol, PEG-60 Lanolin, Phenoxyethanol, Pollen Extract, Polysorbate 20, Propylene Glycol, Sodium Hydroxide, Symphytum Officinale (Comfrey) Leaf Extract, Tilia Cordata Flower Extract, Tocopheryl Acetate, Water

Questions or Comments?

Call toll free 1-855-LIV-GOLD (546-4653)